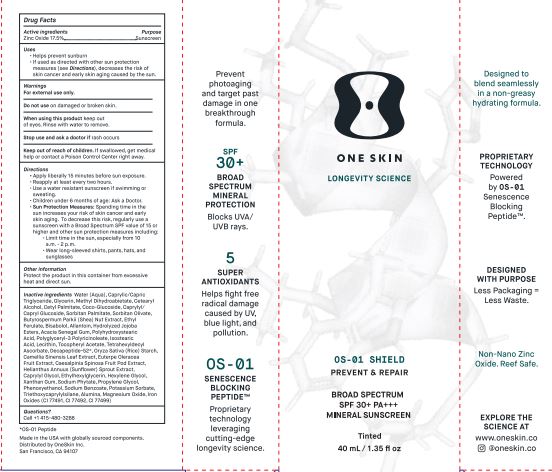 DRUG LABEL: OneSkin OS-01 SHIELD Broad Spectrum SPF 30 Mineral Sunscreen Tinted
NDC: 62742-4228 | Form: CREAM
Manufacturer: Allure Labs
Category: otc | Type: HUMAN OTC DRUG LABEL
Date: 20241209

ACTIVE INGREDIENTS: ZINC OXIDE 17.5 g/100 g
INACTIVE INGREDIENTS: PEPTIDE-T; MEDIUM-CHAIN TRIGLYCERIDES; GLYCERIN; COCO GLUCOSIDE; LEVOMENOL; POTASSIUM SORBATE; STARCH, RICE; CETOSTEARYL ALCOHOL; SORBITAN OLIVATE; ETHYL FERULATE; HELIANTHUS ANNUUS SPROUT; SHEANUT; HYDROLYZED JOJOBA ESTERS (POTASSIUM SALTS); WATER; CETYL PALMITATE; SORBITAN MONOPALMITATE; POLYHYDROXYSTEARIC ACID (2300 MW); POLYGLYCERYL-3 PENTARICINOLEATE; ACAI; CAESALPINIA SPINOSA FRUIT POD; XANTHAN GUM; PROPYLENE GLYCOL; PHENOXYETHANOL; FERROSOFERRIC OXIDE; GREEN TEA LEAF; LECITHIN, SOYBEAN; .ALPHA.-TOCOPHEROL ACETATE; TETRAHEXYLDECYL ASCORBATE; CAPRYLYL GLYCOL; HEXYLENE GLYCOL; PHYTATE SODIUM; TRIETHOXYCAPRYLYLSILANE; MAGNESIUM OXIDE; FERRIC OXIDE RED; SODIUM BENZOATE; ACACIA; ISOSTEARIC ACID; ETHYLHEXYLGLYCERIN; FERRIC OXIDE YELLOW; METHYL DIHYDROABIETATE; CAPRYLYL/CAPRYL OLIGOGLUCOSIDE; ALLANTOIN; ALUMINUM OXIDE

Drug Facts

Active ingredients – Zinc Oxide 17.5 %

Purpose – Sunscreen

Uses –

Helps prevent sunburn
If used as directed with other sun protection measures (See direction), decreases the risk of skin cancer and early skin aging caused by the sun.

WARNINGS

Warning – For external use only

Do not use on damaged or broken skin

When using this product keep out of eye. Rinse with water to remove.

Stop use and ask doctor if rash occurs

Keep out of reach of children. If swallowed, get medical help or contact a poison control center right away.

DOSAGE AND ADMINISTRATION

Direction-

Apply liberally 15 minutes before sun exposure.
Reapply at least every two hours.
Use a water-resistant sunscreen if swimming or sweating.
Children under 6 months of age: Ask a doctor.
Sun protection measures: spending time in the sun increases your risk of skin cancer and early skin aging. To decrease the risk, regularly use a sunscreen with a broad-spectrum value of 15 or higher and other sun protection measures including:
Limit time in the sun. especially from 10 am to 2 pm
Wear long-sleeved shirts, pants hats and sunglasses.

Other information:

Protect the product in this container from excessive heat and direct sun.

Inactive ingredients:

Water(aqua), Caprylic/Capric Triglyceride, Glycerin, Methyl Dihydroabietate, Cetearyl Alcohol, Cetyl Palmitate, Coco-Glucoside, Caprylyl/Capryl Glucoside, Sorbitan Palmitate, Sorbitan Olivate, Butyrospermum Parkii (Shea) Nut Extract, Ethyl Ferulate, Bisabolol, Allantoin, Hydrolyzed Jojoba Esters, Acacia Senegal Gum, Polyhydroxystearic Acid, Polyglyceryl-3 Polyricinoleate, Isostearic Acid, Lecithin, Tocopheryl Acetate, Tetrahexyldecyl Ascorbate, Decapeptide-52*, Oryza Sativa (rice) Starch,Camellia Sinensis Leaf Extract, Euterpe Oleracea Fruit Extract, Caesalpinia Spinosa Fruit Pod Extract, Helianthus Annuus (Sunflower) Sprout Extract, Caprylyl Glycol, Ethylhexylglycerin, Hexylene Glycol, Xanthan Gum, Sodium Phytate, Propylene Glycol, Phenoxyethanol, sodium Benzoate, Potassium Sorbate, Triethoxycaprylylsilane, Alumina, Magnesium Oxide, Iron Oxides (CI 77491, CI 77492, CI77499)